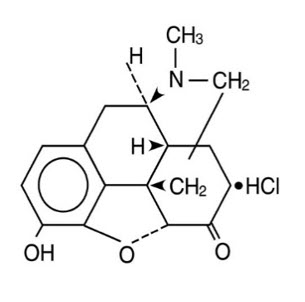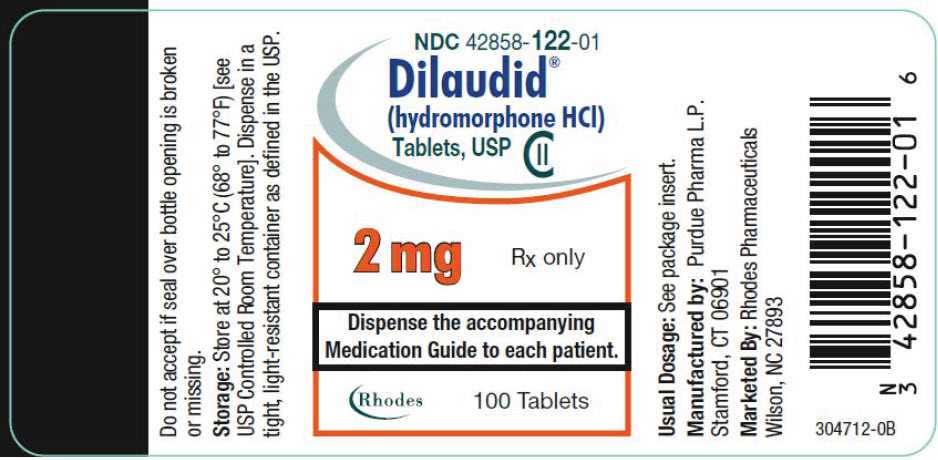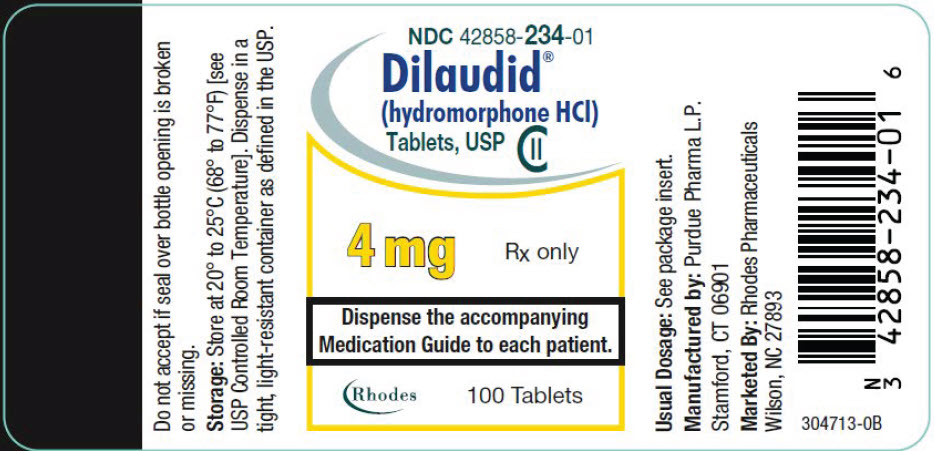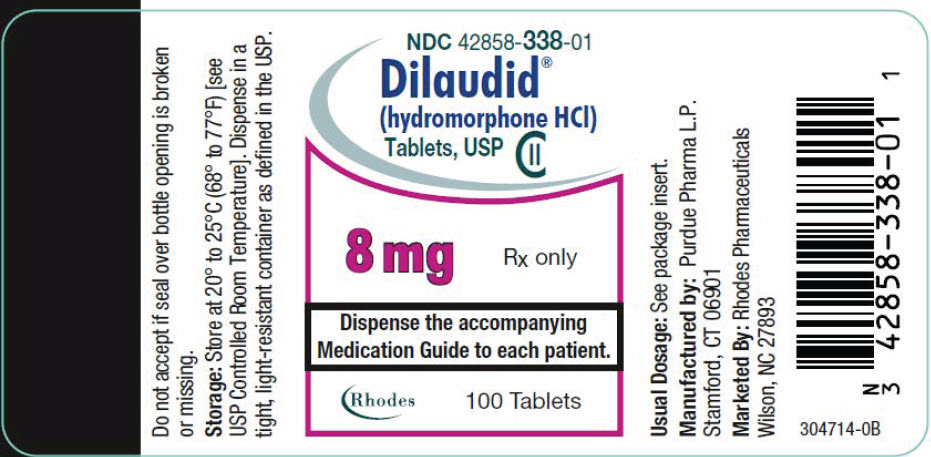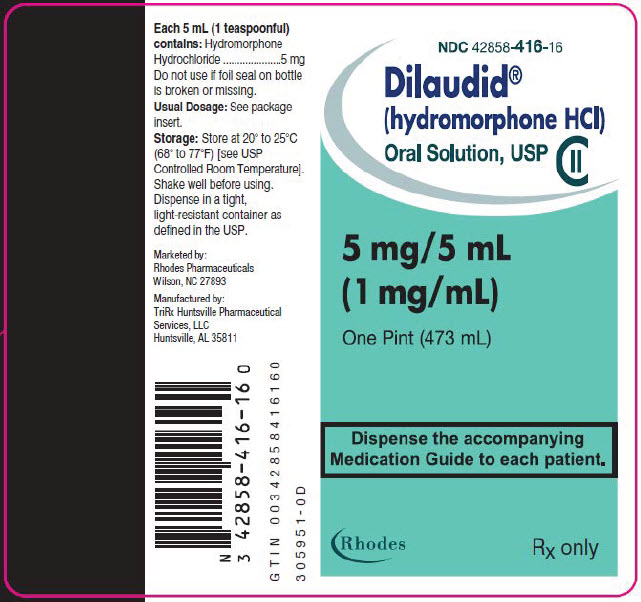 DRUG LABEL: Dilaudid
NDC: 42858-122 | Form: TABLET
Manufacturer: Rhodes Pharmaceuticals L.P.
Category: prescription | Type: HUMAN PRESCRIPTION DRUG LABEL
Date: 20251231
DEA Schedule: CII

ACTIVE INGREDIENTS: hydromorphone hydrochloride 2 mg/1 1
INACTIVE INGREDIENTS: D&C Red No. 30; D&C Yellow No. 10; Anhydrous Lactose; Magnesium Stearate; Sodium metabisulfite

HIGHLIGHTS OF PRESCRIBING INFORMATION

These highlights do not include all the information needed to use DILAUDID® ORAL SOLUTION and DILAUDID® TABLETS safely and effectively. See full prescribing information for DILAUDID® ORAL SOLUTION and DILAUDID® TABLETS.
DILAUDID® (hydromorphone hydrochloride) oral solution
DILAUDID® (hydromorphone hydrochloride) tablets, for oral use, CII
Initial U.S. Approval: January 1984

WARNING: SERIOUS AND LIFE-THREATENING RISKS FROM USE OF DILAUDID

See full prescribing information for complete boxed warning.

- Ensure accuracy when prescribing, dispensing, and administering DILAUDID Oral Solution. Dosing errors due to confusion between mg and mL can result in accidental overdose and death. (2.1, 5.1)
- DILAUDID Oral Solution or DILAUDID Tablets expose users to risks of addiction, abuse, and misuse, which can lead to overdose and death. Assess patient's risk before prescribing and reassess regularly for these behaviors and conditions. (5.2)
- Serious, life-threatening, or fatal respiratory depression may occur, especially upon initiation or following a dosage increase. To reduce the risk of respiratory depression, proper dosing and titration of DILAUDID Oral Solution or DILAUDID Tablets are essential. (5.3)
- Accidental ingestion of DILAUDID Oral Solution or DILAUDID Tablets, especially by children, can result in a fatal overdose of hydromorphone. (5.3)
- Concomitant use of opioids with benzodiazepines or other central nervous system (CNS) depressants, including alcohol, may result in profound sedation, respiratory depression, coma, and death. Reserve concomitant prescribing for use in patients for whom alternative treatment options are inadequate. (5.4, 7)
- Advise pregnant women using opioids for an extended period of time of the risk of Neonatal Opioid Withdrawal Syndrome, which may be life-threatening if not recognized and treated. Ensure that management by neonatology experts will be available at delivery. (5.5)
- Healthcare providers are strongly encouraged to complete a REMS-compliant education program and to counsel patients and caregivers on serious risks, safe use, and the importance of reading the Medication Guide with each prescription. (5.6)

RECENT MAJOR CHANGES

Boxed Warning | 12/2025
Indications and Usage (1) | 12/2025
Dosage and Administration (2.2) | 12/2025
Warning and Precautions (5.2, 5.3, 5.4, 5.12, 5.14) | 12/2025

1 INDICATIONS AND USAGE

DILAUDID Oral Solution and DILAUDID Tablets contain hydromorphone, an opioid agonist, and are indicated for the management of pain severe enough to require an opioid analgesic and for which alternative treatments are inadequate. (1)

Limitations of Use

Because of the risks of addiction, abuse, misuse, overdose, and death, which can occur at any dosage or duration and persist over the course of therapy, reserve opioid analgesics, including DILAUDID Oral Solution or DILAUDID Tablets, for use in patients for whom alternative treatment options are ineffective, not tolerated, or would be otherwise inadequate to provide sufficient management of pain. (1, 5.2)

2 DOSAGE AND ADMINISTRATION

- DILAUDID Oral Solution and DILAUDID Tablets should be prescribed only by healthcare professionals who are knowledgeable about the use of opioids and how to mitigate the associated risks. (2.1)
- Use the lowest effective dosage for the shortest duration of time consistent with individual patient treatment goals. Reserve titration to higher doses of DILAUDID for patients in whom lower doses are insufficiently effective and in whom the expected benefits of using a higher dose opioid clearly outweigh the substantial risks. (2.1, 5)
- Many acute pain conditions (e.g., the pain that occurs with a number of surgical procedures or acute musculoskeletal injuries) require no more than a few days of an opioid analgesic. Clinical guidelines on opioid prescribing for some acute pain conditions are available. (2.1)
- Initiate the dosing regimen for each patient individually, taking into account the patient's underlying cause and severity of pain, prior analgesic treatment and response, and risk factors for addiction, abuse, and misuse. (2.1, 5.2)
- Respiratory depression can occur at any time during opioid therapy, especially when initiating and following dosage increases with DILAUDID. Consider this risk when selecting an initial dose and when making dose adjustments. (2.1, 5.3)
- Discuss opioid overdose reversal agents and options for acquiring them with the patient and/or caregiver, both when initiating and renewing treatment with DILAUDID, especially if the patient has additional risk factors for overdose, or close contacts at risk for exposure and overdose. (2.2, 5.2, 5.3, 5.4)
- Initiate treatment with DILAUDID Oral Solution in a dosing range of 2.5 mL to 10 mL, 2.5 mg to 10 mg, every 3 to 6 hours as needed for pain, and at the lowest dose necessary to achieve adequate analgesia. Titrate the dose based upon the individual patient's response to their initial dose of DILAUDID Oral Solution. (2, 5)
- Initiate treatment with DILAUDID Tablets in a dosing range of 2 mg to 4 mg, orally, every 4 to 6 hours as needed for pain, and at the lowest dose necessary to achieve adequate analgesia. Titrate the dose based upon the individual patient's response to their initial dose of DILAUDID Tablets. (2, 5)
- Periodically reassess patients receiving DILAUDID to evaluate the continued need for opioid analgesics to maintain pain control, for the signs or symptoms of adverse reactions, and for the development of addiction, abuse, or misuse. (2.6)
- Do not rapidly reduce or abruptly discontinue DILAUDID in a physically-dependent patient because rapid reduction or abrupt discontinuation of opioid analgesics has resulted in serious withdrawal symptoms, uncontrolled pain, and suicide. (2.7, 5.14)

3 DOSAGE FORMS AND STRENGTHS

- DILAUDID Oral Solution: 5 mg/5 mL (1 mg/mL)
- DILAUDID Tablets: 2 mg, 4 mg, 8 mg (3)

4 CONTRAINDICATIONS

- Significant respiratory depression. (4)
- Acute or severe bronchial asthma in an unmonitored setting or in absence of resuscitative equipment. (4)
- Known or suspected gastrointestinal obstruction, including paralytic ileus. (4)
- Known hypersensitivity to hydromorphone, hydromorphone salts, or sulfite-containing medications (4)

5 WARNINGS AND PRECAUTIONS

- Opioid-Induced Hyperalgesia and Allodynia: Opioid-Induced Hyperalgesia (OIH) occurs when an opioid analgesic paradoxically causes an increase in pain, or an increase in sensitivity to pain. If OIH is suspected, carefully consider appropriately decreasing the dose of the current opioid analgesic or opioid rotation. (5.7)
- Life-Threatening Respiratory Depression in Patients with Chronic Pulmonary Disease or in Elderly, Cachectic, or Debilitated Patients: Regularly evaluate patients, particularly during initiation and titration. (5.8)
- Adrenal Insufficiency: If diagnosed, treat with physiologic replacement of corticosteroids, and wean patient off of the opioid. (5.9)
- Severe Hypotension: Regularly evaluate patients during dosage initiation and titration. Avoid use of DILAUDID Oral Solution or DILAUDID Tablets in patients with circulatory shock. (5.10)
- Risks of Use in Patients with Increased Intracranial Pressure, Brain Tumors, Head Injury, or Impaired Consciousness: Monitor patients for sedation and respiratory depression. Avoid use of DILAUDID Oral Solution or DILAUDID Tablets in patients with impaired consciousness or coma. (5.11)

6 ADVERSE REACTIONS

Most common adverse reactions are lightheadedness, dizziness, sedation, nausea, vomiting, sweating, flushing, dysphoria, euphoria, dry mouth, and pruritus. (6)

To report SUSPECTED ADVERSE REACTIONS, contact Rhodes Pharmaceuticals at 1-888-827-0616 or FDA at 1-800-FDA-1088 or www.fda.gov/medwatch

7 DRUG INTERACTIONS

- Serotonergic Drugs: Concomitant use may result in serotonin syndrome. Discontinue DILAUDID Oral Solution or DILAUDID Tablets if serotonin syndrome is suspected. (7)
- Monoamine Oxidase Inhibitors (MAOIs): Can potentiate the effects of hydromorphone. Avoid concomitant use in patients receiving MAOIs or within 14 days of stopping treatment with an MAOI. (7)
- Mixed Agonist/Antagonist and Partial Agonist Opioid Analgesics: Avoid use with DILAUDID because they may reduce analgesic effect of DILAUDID or precipitate withdrawal symptoms. (7)

8 USE IN SPECIFIC POPULATIONS

- Pregnancy: May cause fetal harm. (8.1)

FULL PRESCRIBING INFORMATION

WARNING: SERIOUS AND LIFE-THREATENING RISKS FROM USE OF DILAUDID

Risk of Medication Errors

Ensure accuracy when prescribing, dispensing, and administering DILAUDID Oral Solution. Dosing errors due to confusion between mg and mL, and other hydromorphone oral solutions of different concentrations can result in accidental overdose and death [see Dosage and Administration (2.1), Warnings and Precautions (5.1)].

Addiction, Abuse, and Misuse

Because the use of DILAUDID Oral Solution and Dilaudid Tablets expose patients and other users to the risks of opioid addiction, abuse, and misuse, which can lead to overdose and death, assess each patient's risk prior to prescribing and reassess all patients regularly for the development of these behaviors and conditions [see Warnings and Precautions (5.2)].

Life-Threatening Respiratory Depression

Serious, life-threatening, or fatal respiratory depression may occur with use of DILAUDID Oral Solution and DILAUDID Tablets, especially during initiation or following a dosage increase. To reduce the risk of respiratory depression, proper dosing and titration of DILAUDID Oral Solution and DILAUDID Tablets are essential [see Warnings and Precautions (5.3)].

Accidental Ingestion

Accidental ingestion of even one dose of DILAUDID Oral Solution or DILAUDID Tablets, especially by children, can result in a fatal overdose of hydromorphone [see Warnings and Precautions (5.3)].

Risks From Concomitant Use With Benzodiazepines Or Other CNS Depressants

Concomitant use of opioids with benzodiazepines or other central nervous system (CNS) depressants, including alcohol, may result in profound sedation, respiratory depression, coma, and death. Reserve concomitant prescribing of DILAUDID Oral Solution and DILAUDID Tablets and benzodiazepines or other CNS depressants for use in patients for whom alternative treatment options are inadequate [see Warnings and Precautions (5.4), Drug Interactions (7)].

Neonatal Opioid Withdrawal Syndrome (NOWS)

Advise pregnant women using opioids for an extended period of time of the risk of Neonatal Opioid Withdrawal Syndrome, which may be life-threatening if not recognized and treated. Ensure that management by neonatology experts will be available at delivery [see Warnings and Precautions (5.5)].

Opioid Analgesic Risk Evaluation and Mitigation Strategy (REMS)

Healthcare providers are strongly encouraged to complete a REMS-compliant education program and to counsel patients and caregivers on serious risks, safe use, and the importance of reading the Medication Guide with each prescription [see Warnings and Precautions (5.6)].

1 INDICATIONS AND USAGE

DILAUDID Oral Solution and DILAUDID Tablets are indicated for the management of pain severe enough to require an opioid analgesic and for which alternative treatments are inadequate.

Limitations of Use

Because of the risks of addiction, abuse, misuse, overdose, and death, which can occur at any dosage or duration and persist over the course of therapy [see Warnings and Precautions (5.2)], reserve opioid analgesics, including DILAUDID Oral Solution and DILAUDID Tablets, for use in patients for whom alternative treatment options are ineffective, not tolerated, or would be otherwise inadequate to provide sufficient management of pain.

2 DOSAGE AND ADMINISTRATION

2.1 Important Dosage and Administration Instructions

Ensure accuracy when prescribing, dispensing, and administering DILAUDID Oral Solution to avoid dosing errors due to confusion between mg and mL, which could result in accidental overdose and death. Ensure the proper dose is communicated and dispensed. When writing prescriptions, include both the total dose in mg and the total dose in volume.

Instruct patients and caregivers on how to accurately measure and take or administer the correct dose of DILAUDID Oral Solution.

Strongly advise patients and caregivers to always use a graduated oral syringe or measuring cup, with metric units of measurements (i.e., mL), to correctly measure the prescribed amount of medication.

Inform patients and caregivers that oral dosing devices may be obtained from their pharmacy and to never use household teaspoons or tablespoons to measure DILAUDID Oral Solution.

- DILAUDID Oral Solution and DILAUDID Tablets should be prescribed only by healthcare professionals who are knowledgeable about the use of opioids and how to mitigate the associated risks.
- Use the lowest effective dosage for the shortest duration of time consistent with individual patient treatment goals [see Warnings and Precautions (5)]. Because the risk of overdose increases as opioid doses increase, reserve titration to higher doses of DILAUDID Oral Solution and DILAUDID Tablets for patients in whom lower doses are insufficiently effective and in whom the expected benefits of using a higher dose opioid clearly outweigh the substantial risks.
- Many acute pain conditions (e.g., the pain that occurs with a number of surgical procedures or acute musculoskeletal injuries) require no more than a few days of an opioid analgesic. Clinical guidelines on opioid prescribing for some acute pain conditions are available.
- There is variability in the opioid analgesic dose and duration needed to adequately manage pain due both to the cause of pain and to individual patient factors. Initiate the dosing regimen for each patient individually, taking into account the patient's underlying cause and severity of pain, prior analgesic treatment and response, and risk factors for addiction, abuse, and misuse [see Warnings and Precautions (5.2)].
- Respiratory depression can occur at any time during opioid therapy, especially when initiating and following dosage increases with DILAUDID Oral Solution and DILAUDID Tablets. Consider this risk when selecting an initial dose and when making dose adjustments [see Warnings and Precautions (2.1, 5)].
- Initiate treatment with DILAUDID Oral Solution in a dosing range of 2.5 mL to 10 mL, 2.5 mg to 10 mg, every 3 to 6 hours as needed for pain, and at the lowest dose necessary to achieve adequate analgesia. Titrate the dose based upon the individual patient's response to their initial dose of DILAUDID Oral Solution [see Dosage and Administration (2), Warnings and Precautions (5)].
- Initiate treatment with DILAUDID Tablets in a dosing range of 2 mg to 4 mg, orally, every 4 to 6 hours as needed for pain, and at the lowest dose necessary to achieve adequate analgesia. Titrate the dose based upon the individual patient's response to their initial dose of DILAUDID Tablets [see Dosage and Administration (2), Warnings and Precautions (5)].

2.2 Patient Access to an Opioid Overdose Reversal Agent for the Emergency Treatment of Opioid Overdose

Inform patients and caregivers about opioid overdose reversal agents (e.g., naloxone, nalmefene). Discuss the importance of having access to an opioid overdose reversal agent, especially if the patient has risk factors for overdose (e.g., concomitant use of CNS depressants, a history of opioid use disorder, or prior opioid overdose) or if there are household members (including children) or other close contacts at risk for accidental ingestion or opioid overdose. The presence of risk factors for overdose should not prevent the management of pain in any patient [see Warnings and Precautions (5.2, 5.3, 5.4)].

Discuss the options for obtaining an opioid overdose reversal agent (e.g., prescription, over-the-counter, or as part of a community-based program) [see Warnings and Precautions (5.3)].

There are important differences among the opioid overdose reversal agents, such as route of administration, product strength, approved patient age range, and pharmacokinetics. Be familiar with these differences, as outlined in the approved labeling for those products, prior to recommending or prescribing such an agent.

2.3 Initial Dosage

Initiating Treatment with DILAUDID Oral Solution or DILAUDID Tablets

Dilaudid Oral Solution

Initiate treatment with DILAUDID Oral Solution in a dosing range of 2.5 mL to 10 mL, 2.5 mg to 10 mg, every 3 to 6 hours as needed for pain, and at the lowest dose necessary to achieve adequate analgesia. Titrate the dose based upon the individual patient's response to their initial dose of DILAUDID Oral Solution.

Dilaudid Tablets

Initiate treatment with DILAUDID Tablets in a dosing range of 2 mg to 4 mg, orally, every 4 to 6 hours as needed for pain, and at the lowest dose necessary to achieve adequate analgesia. Titrate the dose based upon the individual patient's response to their initial dose of DILAUDID Tablets.

Conversion from Other Opioids to DILAUDID Oral Solution or DILAUDID Tablets

There is inter-patient variability in the potency of opioid drugs and opioid formulations. Therefore, a conservative approach is advised when determining the total daily dosage of DILAUDID Oral Solution or DILAUDID Tablets. It is safer to underestimate a patient's 24-hour DILAUDID dosage than to overestimate the 24-hour dosage and manage an adverse reaction due to overdose.

In general, it is safest to start DILAUDID therapy by administering half of the usual starting dose every 3 to 6 hours for DILAUDID Oral Solution; and every 4 to 6 hours for DILAUDID Tablets. The dose of DILAUDID can be gradually adjusted until adequate pain relief and acceptable side effects have been achieved [see Dosage and Administration (2.5)].

Conversion from DILAUDID Oral Solution or DILAUDID Tablets to Extended-Release Hydromorphone Hydrochloride

The relative bioavailability of DILAUDID Oral Solution and DILAUDID Tablets compared to extended-release hydromorphone is unknown, so conversion to extended-release hydromorphone may lead to increased risk of excessive sedation and respiratory depression.

2.4 Dosage Modifications in Patients with Hepatic Impairment

Initiate treatment with one-fourth to one-half the usual DILAUDID starting dose depending on the degree of impairment [see Use in Specific Populations (8.6), Clinical Pharmacology (12.3)].

2.5 Dosage Modifications in Patients with Renal Impairment

Initiate treatment with one-fourth to one-half the usual DILAUDID starting dose depending on the degree of impairment [see Use in Specific Populations (8.7), Clinical Pharmacology (12.3)].

2.6 Titration and Maintenance of Therapy

Individually titrate DILAUDID Oral Solution or DILAUDID Tablets to a dose that provides adequate analgesia and minimizes adverse reactions. Continually reevaluate patients receiving DILAUDID Oral Solution or DILAUDID Tablets to assess the maintenance of pain control, signs and symptoms of opioid withdrawal, and other adverse reactions, as well as to reassess for the development of addiction, abuse, or misuse [see Warnings and Precautions (5.2, 5.14)]. Frequent communication is important among the prescriber, other members of the healthcare team, the patient, and the caregiver/family during periods of changing analgesic requirements, including initial titration.

If the level of pain increases after dosage stabilization, attempt to identify the source of increased pain before increasing the DILAUDID Oral Solution or DILAUDID Tablets dosage. If after increasing the dosage, unacceptable opioid-related adverse reactions are observed (including an increase in pain after a dosage increase), consider reducing the dosage [see Warnings and Precautions (5)]. Adjust the dosage to obtain an appropriate balance between management of pain and opioid-related adverse reactions.

A supplemental dose of 5 to 15% of the total daily usage may be administered every two hours on an as-needed basis.

2.7 Safe Reduction or Discontinuation of DILAUDID Oral Solution or DILAUDID Tablets

Do not rapidly reduce or abruptly discontinue DILAUDID Oral Solution and DILAUDID Tablets in patients who may be physically dependent on opioids. Rapid reduction or abrupt discontinuation of opioid analgesics in patients who are physically dependent on opioids has resulted in serious withdrawal symptoms, uncontrolled pain, and suicide. Rapid reduction or abrupt discontinuation has also been associated with attempts to find other sources of opioid analgesics, which may be confused with drug-seeking for abuse. Patients may also attempt to treat their pain or withdrawal symptoms with illicit opioids, such as heroin, and other substances.

When a decision has been made to decrease the dose or discontinue therapy in an opioid dependent patient taking DILAUDID Oral Solution and DILAUDID Tablets, there are a variety of factors that should be considered, including the total daily dose of opioid (including DILAUDID Oral Solution and DILAUDID Tablets) the patient has been taking, the duration of treatment, the type of pain being treated, and the physical and psychological attributes of the patient. It is important to ensure ongoing care of the patient and to agree on an appropriate tapering schedule and follow-up plan so that patient and provider goals and expectations are clear and realistic. When opioid analgesics are being discontinued due to a suspected substance use disorder, evaluate and treat the patient, or refer for evaluation and treatment of the substance use disorder. Treatment should include evidence-based approaches, such as medication assisted treatment of opioid use disorder. Complex patients with co-morbid pain and substance use disorders may benefit from referral to a specialist.

There are no standard opioid tapering schedules that are suitable for all patients. Good clinical practice dictates a patient-specific plan to taper the dose of the opioid gradually. For patients on DILAUDID Oral Solution and DILAUDID Tablets who are physically opioid-dependent, initiate the taper by a small enough increment (e.g., no greater than 10% to 25% of the total daily dose) to avoid withdrawal symptoms, and proceed with dose-lowering at an interval of every 2 to 4 weeks. Patients who have been taking opioids for briefer periods of time may tolerate a more rapid taper.

It may be necessary to provide the patient with lower dosage strengths to accomplish a successful taper. Reassess the patient frequently to manage pain and withdrawal symptoms, should they emerge. Common withdrawal symptoms include restlessness, lacrimation, rhinorrhea, yawning, perspiration, chills, myalgia, and mydriasis. Other signs and symptoms also may develop, including irritability, anxiety, backache, joint pain, weakness, abdominal cramps, insomnia, nausea, anorexia, vomiting, diarrhea, or increased blood pressure, respiratory rate, or heart rate. If withdrawal symptoms arise, it may be necessary to pause the taper for a period of time or raise the dose of the opioid analgesic to the previous dose, and then proceed with a slower taper. In addition, evaluate patients for any changes in mood, emergence of suicidal thoughts, or use of other substances.

When managing patients taking opioid analgesics, particularly those who have been treated for an extended period of time, and/or with high doses for chronic pain, ensure that a multimodal approach to pain management, including mental health support (if needed), is in place prior to initiating an opioid analgesic taper. A multimodal approach to pain management may optimize the treatment of chronic pain, as well as assist with the successful tapering of the opioid analgesic [see Warnings and Precautions (5.14), Drug Abuse and Dependence (9.3)].

3 DOSAGE FORMS AND STRENGTHS

DILAUDID Oral Solution: 5 mg/5 mL (1 mg/mL) of hydromorphone hydrochloride in a clear, colorless to pale yellow, slightly viscous liquid.

DILAUDID Tablets:

- 2 mg tablets (light orange, round, flat-faced tablets, with beveled edges, debossed with a "P" on one side and the number "2" on the opposite side)
- 4 mg tablets (light yellow, round, flat-faced tablets, with beveled edges, debossed with a "P" on one side and the number "4" on the opposite side)
- 8 mg tablets (white, triangular shaped tablets, debossed with a "P" and an inverted "P" separated with a bisect on one side of the tablet and debossed with the number "8" on the other side of the tablet)

4 CONTRAINDICATIONS

DILAUDID Oral Solution and DILAUDID Tablets are contraindicated in patients with:

- Significant respiratory depression [see Warnings and Precautions (5.3)]
- Acute or severe bronchial asthma in an unmonitored setting or in the absence of resuscitative equipment [see Warnings and Precautions (5.8)]
- Known or suspected gastrointestinal obstruction, including paralytic ileus [see Warnings and Precautions (5.12)]
- Hypersensitivity to hydromorphone, hydromorphone salts, any other components of the product, or sulfite-containing medications (e.g., anaphylaxis) [see Warnings and Precautions (5.16), Adverse Reactions (6.1)]

5 WARNINGS AND PRECAUTIONS

5.1 Risk of Accidental Overdose and Death due to Medication Errors

Dosing errors can result in accidental overdose and death. Avoid dosing errors that may result from confusion between mg and mL and confusion with other hydromorphone oral solutions of different concentrations, when prescribing, dispensing, and administering DILAUDID Oral Solution. Ensure that the dose is communicated clearly and dispensed accurately.

Instruct patients and caregivers on how to measure and take or administer the correct dose of DILAUDID Oral Solution and to use extreme caution when measuring the dose. Strongly advise patients and caregivers to obtain and always use a graduated device that can measure and deliver the prescribed dose accurately, and to never use household teaspoons or tablespoons to measure a dose because these are not accurate measuring devices.

5.2 Addiction, Abuse, and Misuse

DILAUDID Oral Solution and DILAUDID Tablets contain hydromorphone, a Schedule II controlled substance. As an opioid, DILAUDID exposes users to the risks of addiction, abuse, and misuse [see Drug Abuse and Dependence (9)].

Although the risk of addiction in any individual is unknown, it can occur in patients appropriately prescribed DILAUDID Oral Solution or DILAUDID Tablets. Addiction can occur at recommended doses and if the drug is misused or abused. The risk of opioid-related overdose or overdose-related death is increased with higher opioid doses, and this risk persists over the course of therapy. In postmarketing studies, addiction, abuse, misuse, and fatal and non-fatal opioid overdose were observed in patients with long-term opioid use [see Adverse Reactions (6.2)].

Assess each patient's risk for opioid addiction, abuse, or misuse prior to prescribing DILAUDID Oral Solution or DILAUDID Tablets, and reassess all patients receiving DILAUDID Oral Solution or DILAUDID Tablets for the development of these behaviors and conditions. Risks are increased in patients with a personal or family history of substance abuse (including drug or alcohol abuse or addiction) or mental illness (e.g., major depression). The potential for these risks should not, however, prevent the proper management of pain in any given patient. Patients at increased risk may be prescribed opioids such as DILAUDID Oral Solution or DILAUDID Tablets but use in such patients necessitates intensive counseling about the risks and proper use of DILAUDID Oral Solution and DILAUDID Tablets along with frequent reevaluation for signs of addiction, abuse, and misuse. Consider recommending or prescribing an opioid overdose reversal agent [see Dosage and Administration (2.2), Warnings and Precautions (5.3)].

Opioids are sought for nonmedical use and are subject to diversion from legitimate prescribed use. Consider these risks when prescribing or dispensing DILAUDID Oral Solution or DILAUDID Tablets. Strategies to reduce these risks include prescribing the drug in the smallest appropriate quantity and advising the patient on careful storage of the drug during the course of treatment and the proper disposal of unused drug. Contact local state professional licensing board or state-controlled substances authority for information on how to prevent and detect abuse or diversion of this product.

5.3 Life-Threatening Respiratory Depression

Serious, life-threatening, or fatal respiratory depression has been reported with the use of opioids, even when used as recommended. Respiratory depression, if not immediately recognized and treated, may lead to respiratory arrest and death. Management of respiratory depression may include close observation, supportive measures, and use of opioid overdose reversal agents (e.g., naloxone, nalmefene), depending on the patient's clinical status [see Overdosage (10)]. Carbon dioxide (CO2) retention from opioid-induced respiratory depression can exacerbate the sedating effects of opioids.

While serious, life-threatening, or fatal respiratory depression can occur at any time during the use of DILAUDID Oral Solution or DILAUDID Tablets, the risk is greatest during the initiation of therapy or following a dosage increase.

To reduce the risk of respiratory depression, proper dosing and titration of DILAUDID Oral Solution or DILAUDID Tablets are essential [see Dosage and Administration (2)]. Overestimating the DILAUDID Oral Solution or DILAUDID Tablets dosage when converting patients from another opioid product can result in a fatal overdose with the first dose.

Accidental ingestion of even one dose of DILAUDID Oral Solution or DILAUDID Tablets, especially by children, can result in respiratory depression and death due to an overdose of hydromorphone.

Educate patients and caregivers on how to recognize respiratory depression and emphasize the importance of calling 911 or getting emergency medical help right away in the event of a known or suspected overdose.

Opioids can cause sleep-related breathing disorders including central sleep apnea (CSA) and sleep-related hypoxemia. Opioid use increases the risk of CSA in a dose-dependent fashion. In patients who present with CSA, consider decreasing the opioid dosage using best practices for opioid taper [see Dosage and Administration (2.7)].

Patient Access to an Opioid Overdose Reversal Agent for the Emergency Treatment of Opioid Overdose

Inform patients and caregivers about opioid overdose reversal agents (e.g., naloxone, nalmefene). Discuss the importance of having access to an opioid overdose reversal agent, especially if the patient has risk factors for overdose (e.g., concomitant use of CNS depressants, a history of opioid use disorder, or prior opioid overdose) or if there are household members (including children) or other close contacts at risk for accidental ingestion or opioid overdose. The presence of risk factors for overdose should not prevent the management of pain in any patient [see Warnings and Precautions (5.2, 5.4)]. Discuss the options for obtaining an opioid overdose reversal agent (e.g., prescription, over-the-counter, or as part of a community-based program).

There are important differences among the opioid overdose reversal agents, such as route of administration, product strength, approved patient age range, and pharmacokinetics. Be familiar with these differences, as outlined in the approved labeling for those products, prior to recommending or prescribing such an agent.

Educate patients and caregivers on how to recognize respiratory depression, and how to use an opioid overdose reversal agent for the emergency treatment of opioid overdose. Emphasize the importance of calling 911 or getting emergency medical help, even if an opioid overdose reversal agent is administered [see Dosage and Administration (2.2), Warnings and Precautions (5.2, 5.4), Overdosage (10)].

5.4 Risks from Concomitant Use with Benzodiazepines or Other CNS Depressants

Profound sedation, respiratory depression, coma, and death may result from the concomitant use of DILAUDID Oral Solution and DILAUDID Tablets with benzodiazepines and/or other CNS depressants, including alcohol (e.g., non-benzodiazepine sedatives/hypnotics, anxiolytics, tranquilizers, muscle relaxants, general anesthetics, antipsychotics, gabapentinoids [gabapentin or pregabalin], and other opioids). Because of these risks, reserve concomitant prescribing of these drugs for use in patients for whom alternative treatment options are inadequate.

Observational studies have demonstrated that concomitant use of opioid analgesics and benzodiazepines increases the risk of drug-related mortality compared to use of opioid analgesics alone. Because of similar pharmacological properties, it is reasonable to expect similar risk with the concomitant use of other CNS depressant drugs with opioid analgesics [see Drug Interactions (7)].

If the decision is made to prescribe a benzodiazepine or other CNS depressant concomitantly with an opioid analgesic, prescribe the lowest effective dosages and minimum durations of concomitant use. In patients already receiving an opioid analgesic, prescribe a lower initial dose of the benzodiazepine or other CNS depressant than indicated in the absence of an opioid, and titrate based on clinical response. If an opioid analgesic is initiated in a patient already taking a benzodiazepine or other CNS depressant, prescribe a lower initial dose of the opioid analgesic, and titrate based on clinical response. Inform patients and caregivers of this potential interaction and educate then on the signs and symptoms of respiratory depression (including sedation).

If concomitant use is warranted, consider recommending or prescribing an opioid overdose reversal agent [see Dosage and Administration (2.2), Warnings and Precautions (5.3), Overdosage (10)].

Advise both patients and caregivers about the risks of respiratory depression and sedation when DILAUDID Oral Solution or DILAUDID Tablets are used with benzodiazepines or other CNS depressants (including alcohol and illicit drugs). Advise patients not to drive or operate heavy machinery until the effects of concomitant use of the benzodiazepine or other CNS depressant have been determined. Screen patients for risk of substance use disorders, including opioid abuse and misuse, and warn them of the risk for overdose and death associated with the use of additional CNS depressants including alcohol and illicit drugs [see Drug Interactions (7)].

5.5 Neonatal Opioid Withdrawal Syndrome

Use of DILAUDID Oral Solution or DILAUDID Tablets for an extended period of time during pregnancy can result in withdrawal in the neonate. Neonatal opioid withdrawal syndrome, unlike opioid withdrawal syndrome in adults, may be life-threatening if not recognized and treated, and requires management according to protocols developed by neonatology experts. Observe newborns for signs of neonatal opioid withdrawal syndrome and manage accordingly. Advise pregnant women using opioids for an extended period of time of the risk of neonatal opioid withdrawal syndrome and ensure that appropriate treatment will be available [see Use in Specific Populations (8.1)].

5.6 Opioid Analgesic Risk Evaluation and Mitigation Strategy (REMS)

To ensure that the benefits of opioid analgesics outweigh the risks of addiction, abuse, and misuse, the Food and Drug Administration (FDA) has required a Risk Evaluation and Mitigation Strategy (REMS) for these products. Under the requirements of the REMS, drug companies with approved opioid analgesic products must make REMS-compliant education programs available to healthcare providers. Healthcare providers are strongly encouraged to do all of the following:

- Complete a REMS-compliant education program offered by an accredited provider of continuing education (CE) or another education program that includes all the elements of the FDA Education Blueprint for Health Care Providers Involved in the Management or Support of Patients with Pain.
- Discuss the safe use, serious risks, and proper storage and disposal of opioid analgesics with patients and/or their caregivers every time these medicines are prescribed. The Patient Counseling Guide (PCG) can be obtained at this link: www.fda.gov/OpioidAnalgesicREMSPCG.
- Emphasize to patients and their caregivers the importance of reading the Medication Guide that they will receive from their pharmacist every time an opioid analgesic is dispensed to them.
- Consider using other tools to improve patient, household, and community safety, such as patient-prescriber agreements that reinforce patient-prescriber responsibilities.

To obtain further information on the opioid analgesic REMS and for a list of accredited REMS CME/CE, call 1-800-503-0784, or log on to www.opioidanalgesicrems.com. The FDA Blueprint can be found at www.fda.gov/OpioidAnalgesicREMSBlueprint.

5.7 Opioid-Induced Hyperalgesia and Allodynia

Opioid-Induced Hyperalgesia (OIH) occurs when an opioid analgesic paradoxically causes an increase in pain, or an increase in sensitivity to pain. This condition differs from tolerance, which is the need for increasing doses of opioids to maintain a defined effect [see Dependence (9.3)]. Symptoms of OIH include (but may not be limited to) increased levels of pain upon opioid dosage increase, decreased levels of pain upon opioid dosage decrease, or pain from ordinarily non-painful stimuli (allodynia). These symptoms may suggest OIH only if there is no evidence of underlying disease progression, opioid tolerance, opioid withdrawal, or addictive behavior.

Cases of OIH have been reported, both with short-term and longer-term use of opioid analgesics. Though the mechanism of OIH is not fully understood, multiple biochemical pathways have been implicated. Medical literature suggests a strong biologic plausibility between opioid analgesics and OIH and allodynia. If a patient is suspected to be experiencing OIH, carefully consider appropriately decreasing the dose of the current opioid analgesic or opioid rotation (safely switching the patient to a different opioid moiety) [see Dosage and Administration (2.7), Warnings and Precautions (5.14)].

5.8 Life-Threatening Respiratory Depression in Patients with Chronic Pulmonary Disease or in Elderly, Cachectic, or Debilitated Patients

The use of DILAUDID Oral Solution or DILAUDID Tablets in patients with acute or severe bronchial asthma in an unmonitored setting or in the absence of resuscitative equipment is contraindicated.

Patients with Chronic Pulmonary Disease: DILAUDID Oral Solution- or DILAUDID Tablet-treated patients with significant chronic obstructive pulmonary disease or cor pulmonale, and those with a substantially decreased respiratory reserve, hypoxia, hypercapnia, or pre-existing respiratory depression are at increased risk of decreased respiratory drive including apnea, even at recommended dosages of DILAUDID Oral Solution or DILAUDID Tablets [see Warnings and Precautions (5.3)].

Elderly, Cachectic, or Debilitated Patients: Life-threatening respiratory depression is more likely to occur in elderly, cachectic, or debilitated patients because they may have altered pharmacokinetics or altered clearance compared to younger, healthier patients [see Warnings and Precautions (5.3)].

Regularly evaluate patients, particularly when initiating and titrating DILAUDID Oral Solution or DILAUDID Tablets and when DILAUDID is given concomitantly with other drugs that depress respiration [see Warnings and Precautions (5.3, 5.4), Drug Interactions (7)]. Alternatively, consider the use of non-opioid analgesics in these patients.

5.9 Adrenal Insufficiency

Cases of adrenal insufficiency have been reported with opioid use, more often following greater than one month of use. Presentation of adrenal insufficiency may include non-specific symptoms and signs including nausea, vomiting, anorexia, fatigue, weakness, dizziness, and low blood pressure. If adrenal insufficiency is suspected, confirm the diagnosis with diagnostic testing as soon as possible. If adrenal insufficiency is diagnosed, treat with physiologic replacement doses of corticosteroids. Wean the patient off of the opioid to allow adrenal function to recover and continue corticosteroid treatment until adrenal function recovers. Other opioids may be tried as some cases reported use of a different opioid without recurrence of adrenal insufficiency. The information available does not identify any particular opioids as being more likely to be associated with adrenal insufficiency.

5.10 Severe Hypotension

DILAUDID Oral Solution or DILAUDID Tablets may cause severe hypotension including orthostatic hypotension and syncope in ambulatory patients. There is increased risk in patients whose ability to maintain blood pressure has already been compromised by a reduced blood volume or concurrent administration of certain CNS depressant drugs (e.g. phenothiazines or general anesthetics) [see Drug Interactions (7)]. Regularly evaluate these patients for signs of hypotension after initiating or titrating the dosage of DILAUDID Oral Solution or DILAUDID Tablets. In patients with circulatory shock, DILAUDID may cause vasodilation that can further reduce cardiac output and blood pressure. Avoid the use of DILAUDID Oral Solution or DILAUDID Tablets in patients with circulatory shock.

5.11 Risks of Use in Patients with Increased Intracranial Pressure, Brain Tumors, Head Injury, or Impaired Consciousness

In patients who may be susceptible to the intracranial effects of CO2 retention (e.g., those with evidence of increased intracranial pressure or brain tumors), DILAUDID Oral Solution or DILAUDID Tablets may reduce respiratory drive, and the resultant CO2 retention can further increase intracranial pressure. Monitor such patients for signs of sedation and respiratory depression, particularly when initiating therapy with DILAUDID Oral Solution or DILAUDID Tablets.

Opioids may also obscure the clinical course in a patient with a head injury. Avoid the use of DILAUDID in patients with impaired consciousness or coma.

5.12 Risks of Gastrointestinal Complications

DILAUDID Oral Solution or DILAUDID Tablets are contraindicated in patients with known or suspected gastrointestinal obstruction, including paralytic ileus.

The hydromorphone in DILAUDID Oral Solution or DILAUDID Tablets may cause spasm of the sphincter of Oddi. Opioids may cause increases in serum amylase. Regularly evaluate patients with biliary tract disease, including acute pancreatitis, for worsening symptoms.

Cases of opioid-induced esophageal dysfunction (OIED) have been reported in patients taking opioids. The risk of OIED may increase as the dose and/or duration of opioids increases. Regularly evaluate patients for signs and symptoms of OIED (e.g., dysphagia, regurgitation, non-cardiac chest pain) and, if necessary, adjust opioid therapy as clinically appropriate [see Clinical Pharmacology (12.2)].

5.13 Increased Risk of Seizures in Patients with Seizure Disorders

The hydromorphone in DILAUDID Oral Solution or DILAUDID Tablets may increase the frequency of seizures in patients with seizure disorders, and may increase the risk of seizures occurring in other clinical settings associated with seizures. Regularly evaluate patients with a history of seizure disorders for worsened seizure control during DILAUDID Oral Solution or DILAUDID Tablets therapy.

5.14 Withdrawal

Do not rapidly reduce or abruptly discontinue DILAUDID Oral Solution or DILAUDID Tablets in a patient physically dependent on opioids. When discontinuing DILAUDID Oral Solution or DILAUDID Tablets in a physically dependent patient, gradually taper the dosage. Rapid tapering of hydromorphone in a patient physically dependent on opioids may lead to a withdrawal syndrome and return of pain [see Dosage and Administration (2.7), Drug Abuse and Dependence (9.3)].

Additionally, avoid the use of mixed agonist/antagonist (e.g., pentazocine, nalbuphine, and butorphanol) or partial agonist (e.g., buprenorphine) analgesics in patients who are receiving a full opioid agonist analgesic, including DILAUDID Oral Solution or DILAUDID Tablets. In these patients, mixed agonist/antagonist and partial agonist analgesics may reduce the analgesic effect and/or precipitate withdrawal symptoms [see Drug Interactions (7)].

5.15 Risks of Driving and Operating Machinery

DILAUDID Oral Solution or DILAUDID Tablets may impair the mental or physical abilities needed to perform potentially hazardous activities such as driving a car or operating machinery. Warn patients not to drive or operate dangerous machinery unless they are tolerant to the effects of DILAUDID Oral Solution or DILAUDID Tablets and know how they will react to the medication.

5.16 Sulfites

DILAUDID Oral Solution and DILAUDID Tablets contain sodium metabisulfite, a sulfite that may cause allergic-type reactions including anaphylactic symptoms and life-threatening or less severe asthmatic episodes in certain susceptible people. The overall prevalence of sulfite sensitivity in the general population is unknown and probably low. Sulfite sensitivity is seen more frequently in asthmatic than in nonasthmatic people. Use of DILAUDID Oral Solution and DILAUDID Tablets is contraindicated in patients with hypersensitivity to sulfite-containing medications.

6 ADVERSE REACTIONS

The following serious adverse reactions are described, or described in greater detail, in other sections:

- Addiction, Abuse, and Misuse [see Warnings and Precautions (5.2)]
- Life-Threatening Respiratory Depression [see Warnings and Precautions (5.3)]
- Interactions with Benzodiazepines or Other CNS Depressants [see Warnings and Precautions (5.4)]
- Neonatal Opioid Withdrawal Syndrome [see Warnings and Precautions (5.5)]
- Opioid-Induced Hyperalgesia and Allodynia [see Warnings and Precautions (5.7)]
- Adrenal Insufficiency [see Warnings and Precautions (5.9)]
- Severe Hypotension [see Warnings and Precautions (5.10)]
- Gastrointestinal Adverse Reactions [see Warnings and Precautions (5.12)]
- Seizures [see Warnings and Precautions (5.13)]
- Withdrawal [see Warnings and Precautions (5.14)]

6.1 Clinical Trials Experience

Because clinical trials are conducted under widely varying conditions, adverse reaction rates observed in the clinical trials of a drug cannot be directly compared to rates in the clinical trials of another drug and may not reflect the rates observed in clinical practice.

Serious adverse reactions associated with DILAUDID include respiratory depression and apnea and, to a lesser degree, circulatory depression, respiratory arrest, shock, and cardiac arrest.

The most common adverse effects are lightheadedness, dizziness, sedation, nausea, vomiting, sweating, flushing, dysphoria, euphoria, dry mouth, and pruritus. These effects seem to be more prominent in ambulatory patients and in those not experiencing severe pain.

Less Frequently Observed Adverse Reactions

Cardiac disorders: tachycardia, bradycardia, palpitations

Eye disorders: vision blurred, diplopia, miosis, visual impairment

Gastrointestinal disorders: constipation, ileus, diarrhea, abdominal pain

General disorders and administration site conditions: weakness, feeling abnormal, chills

Hepatobiliary disorders: biliary colic

Metabolism and nutrition disorders: decreased appetite

Musculoskeletal and connective tissue disorders: muscle rigidity

Nervous system disorders: headache, tremor, paraesthesia, nystagmus, increased intracranial pressure, syncope, taste alteration, involuntary muscle contractions, presyncope

Psychiatric disorders: agitation, mood altered, nervousness, anxiety, depression, hallucination, disorientation, insomnia, abnormal dreams

Renal and urinary disorders: urinary retention, urinary hesitation, antidiuretic effects

Respiratory, thoracic, and mediastinal disorders: bronchospasm, laryngospasm

Skin and subcutaneous tissue disorders: urticaria, rash, hyperhidrosis

Vascular disorders: flushing, hypotension, hypertension

6.2 Postmarketing Experience

The following adverse reactions have been identified during post approval use of hydromorphone. Because these reactions are reported voluntarily from a population of uncertain size, it is not always possible to reliably estimate their frequency or establish a causal relationship to drug exposure.

Confusional state, convulsions, drowsiness, dyskinesia, dyspnea, erectile dysfunction, fatigue, hepatic enzymes increased, hyperalgesia, hypersensitivity reaction, lethargy, myoclonus, oropharyngeal swelling, peripheral edema, and somnolence.

Serotonin syndrome: Cases of serotonin syndrome, a potentially life-threatening condition, have been reported during concomitant use of opioids with serotonergic drugs.

Adrenal insufficiency: Cases of adrenal insufficiency have been reported with opioid use, more often following greater than one month of use.

Anaphylaxis: Anaphylaxis has been reported with ingredients contained in DILAUDID Oral Solution or DILAUDID Tablets.

Androgen deficiency: Cases of androgen deficiency have occurred with use of opioids for an extended period of time [see Clinical Pharmacology (12.2)].

Hyperalgesia and Allodynia: Cases of hyperalgesia and allodynia have been reported with opioid therapy of any duration [see Warnings and Precautions (5.7)].

Hypoglycemia: Cases of hypoglycemia have been reported in patients taking opioids. Most reports were in patients with at least one predisposing risk factor (e.g., diabetes).

Opioid-induced esophageal dysfunction (OIED): Cases of OIED have been reported in patients taking opioids and may occur more frequently in patients taking higher doses of opioids, and/or in patients taking opioids longer term [see Warnings and Precautions (5.12)].

Adverse Reactions from Observational Studies

A prospective, observational cohort study estimated the risks of addiction, abuse, and misuse in patients initiating long-term use of Schedule II opioid analgesics between 2017 and 2021. Study participants included in one or more analyses had been enrolled in selected insurance plans or health systems for at least one year, were free of at least one outcome at baseline, completed a minimum number of follow-up assessments, and either: 1) filled multiple extended-release/long-acting opioid analgesic prescriptions during a 90-day period (n=978); or 2) filled any Schedule II opioid analgesic prescriptions covering at least 70 of 90 days (n=1,244). Those included also had no dispensing of the qualifying opioids in the previous 6 months.

Over 12 months:

- approximately 1% to 6% of participants across the two cohorts newly met criteria for addiction, as assessed with two validated interview-based measures of moderate-to-severe opioid use disorder based on Diagnostic and Statistical Manual of Mental Disorders, Fifth Edition (DSM-5) criteria, and
- approximately 9% and 22% of participants across the two cohorts newly met criteria for prescription opioid abuse and misuse [defined in Drug Abuse and Dependence (9.2)], respectively, as measured with a validated self-reported instrument.

A retrospective, observational cohort study estimated the risk of opioid-involved overdose or opioid overdose-related death in patients with new long-term use of Schedule II opioid analgesics from 2006 through 2016 (n=220,249). Included patients had been enrolled in either one of two commercial insurance programs, one managed care program, or one Medicaid program for at least 9 months. New long-term use was defined as having Schedule II opioid analgesic prescriptions covering at least 70 days' supply over the 3 months prior to study entry and none during the preceding 6 months. Patients were excluded if they had an opioid-involved overdose in the 9 months prior to study entry. Overdose was measured using a validated medical code-based algorithm with linkage to the National Death Index database. The 5-year cumulative incidence estimates for opioid-involved overdose or opioid overdose-related death ranged from approximately 1.5% to 4% across study sites, counting only the first event during follow-up. Approximately 17% of first opioid overdoses observed over the entire study period (5 to 11 years, depending on the study site) were fatal. Higher baseline opioid dose was the strongest and most consistent predictor of opioid-involved overdose or opioid overdose-related death. Study exclusion criteria may have selected patients at lower risk of overdose, and substantial loss to follow-up (approximately 80%) also may have biased estimates.

The risk estimates from the studies described above may not be generalizable to all patients receiving opioid analgesics, such as those with exposures shorter or longer than the duration evaluated in the studies.

7 DRUG INTERACTIONS

Table 1 includes clinically significant drug interactions with DILAUDID.

Table 1: Clinically Significant Drug Interactions with DILAUDID
Benzodiazepines and other Central Nervous System (CNS) Depressants
Clinical Impact: | Due to additive pharmacologic effect, the concomitant use of benzodiazepines or other CNS depressants, including alcohol, can increase the risk of hypotension, respiratory depression, profound sedation, coma, and death [see Warnings and Precautions (5.4)].
Intervention: | Reserve concomitant prescribing of these drugs for use in patients for whom alternative treatment options are inadequate. Limit dosages and durations to the minimum required. Inform patients and caregivers of this potential interaction and educate them on the signs and symptoms of respiratory depression (including sedation). If concomitant use is warranted, consider recommending or prescribing an opioid overdose reversal agent [see Dosage and Administration (2.2), Warnings and Precautions (5.2, 5.3, 5.4)].
Examples: | Benzodiazepines and other sedatives/hypnotics, anxiolytics, tranquilizers, muscle relaxants, general anesthetics, antipsychotics, gabapentinoids (gabapentin or pregabalin), other opioids, alcohol.
Serotonergic Drugs
Clinical Impact: | The concomitant use of opioids with other drugs that affect the serotonergic neurotransmitter system has resulted in serotonin syndrome.
Intervention: | If concomitant use is warranted, frequently evaluate the patient, particularly during treatment initiation and dose adjustment. Discontinue DILAUDID Oral Solution or DILAUDID Tablets if serotonin syndrome is suspected.
Examples: | Selective serotonin reuptake inhibitors (SSRIs), serotonin and norepinephrine reuptake inhibitors (SNRIs), tricyclic antidepressants (TCAs), triptans, 5-HT3 receptor antagonists, drugs that affect the serotonin neurotransmitter system (e.g., mirtazapine, trazodone, tramadol), certain muscle relaxants (i.e., cyclobenzaprine, metaxalone), monoamine oxidase (MAO) inhibitors (those intended to treat psychiatric disorders and also others, such as linezolid and intravenous methylene blue).
Monoamine Oxidase Inhibitors (MAOIs)
Clinical Impact: | MAOI interactions with opioids may manifest as serotonin syndrome or opioid toxicity (e.g., respiratory depression, coma) [see Warnings and Precautions (5.3)]. If urgent use of an opioid is necessary, use test doses and frequent titration of small doses to treat pain while closely monitoring blood pressure and signs and symptoms of CNS and respiratory depression.
Intervention: | The use of DILAUDID Oral Solution or DILAUDID Tablets is not recommended for patients taking MAOIs or within 14 days of stopping such treatment.
Examples: | Phenelzine, tranylcypromine, and linezolid.
Mixed Agonist/Antagonist and Partial Agonist Opioid Analgesics
Clinical Impact: | May reduce the analgesic effect of DILAUDID Oral Solution or DILAUDID Tablets and/or precipitate withdrawal symptoms.
Intervention: | Avoid concomitant use.
Examples: | Butorphanol, nalbuphine, pentazocine, and buprenorphine.
Muscle Relaxants
Clinical Impact: | Hydromorphone may enhance the neuromuscular blocking action of skeletal muscle relaxants and produce an increased degree of respiratory depression.
Intervention: | Because respiratory depression may be greater than otherwise expected, decrease the dosage of DILAUDID Oral Solution or DILAUDID Tablets and/or the muscle relaxant as necessary. Due to the risk of respiratory depression with concomitant use of skeletal muscle relaxants and opioids, consider recommending or prescribing an opioid overdose reversal agent [see Dosage and Administration (2.2), Warnings and Precautions (5.3, 5.4)].
Examples: | cyclobenzaprine, metaxalone
Diuretics
Clinical Impact: | Opioids can reduce the efficacy of diuretics by inducing the release of antidiuretic hormone.
Intervention: | Evaluate patients for signs of diminished diuresis and/or effects on blood pressure and increase the dosage of the diuretic as needed.
Anticholinergic Drugs
Clinical Impact: | The concomitant use of anticholinergic drugs may increase risk of urinary retention and/or severe constipation, which may lead to paralytic ileus.
Intervention: | Evaluate patients for signs of urinary retention or reduced gastric motility when DILAUDID Oral Solution or DILAUDID Tablets is used concomitantly with anticholinergic drugs.

8 USE IN SPECIFIC POPULATIONS

8.1 Pregnancy

Risk Summary

Use of opioid analgesics for an extended period of time during pregnancy may cause neonatal opioid withdrawal syndrome [see Warnings and Precautions (5.5)]. There are no available data with DILAUDID in pregnant women to inform a drug-associated risk for major birth defects and miscarriage.

In animal reproduction studies, reduced postnatal survival of pups, and decreased were noted following oral treatment of pregnant rats with hydromorphone during gestation and through lactation at doses 0.8 times the human daily dose of 24 mg/day (HDD), respectively. In published studies, neural tube defects were noted following subcutaneous injection of hydromorphone to pregnant hamsters at doses 6.4 times the HDD and soft tissue and skeletal abnormalities were noted following subcutaneous continuous infusion of 3 times the HDD to pregnant mice. No malformations were noted at 4 or 40.5 times the HDD in pregnant rats or rabbits, respectively [see Data]. Based on animal data, advise pregnant women of the potential risk to a fetus.

The background risk of major birth defects and miscarriage for the indicated population is unknown. All pregnancies have a background risk of birth defect, loss, or other adverse outcomes. In the U.S. general population, the estimated background risk of major birth defects and miscarriage in clinically recognized pregnancies is 2 to 4% and 15 to 20%, respectively.

Clinical Considerations

Fetal/Neonatal Adverse Reactions

Use of opioid analgesics for an extended period of time during pregnancy for medical or nonmedical purposes can result in physical dependence in the neonate and neonatal opioid withdrawal syndrome shortly after birth.

Neonatal opioid withdrawal syndrome presents as irritability, hyperactivity and abnormal sleep pattern, high pitched cry, tremor, vomiting, diarrhea, and failure to gain weight. The onset, duration, and severity of neonatal opioid withdrawal syndrome vary based on the specific opioid used, duration of use, timing and amount of last maternal use, and rate of elimination of the drug by the newborn. Observe newborns for symptoms of neonatal opioid withdrawal syndrome and manage accordingly [see Warnings and Precautions (5.5)].

Labor or Delivery

Opioids cross the placenta and may produce respiratory depression and psycho-physiologic effects in neonates. An opioid overdose reversal agent, such as naloxone or nalmefene, must be available for reversal of opioid-induced respiratory depression in the neonate. DILAUDID Oral Solution or DILAUDID Tablets is not recommended for use in pregnant women during or immediately prior to labor, when other analgesic techniques are more appropriate. Opioid analgesics, including DILAUDID Oral Solution or DILAUDID Tablets, can prolong labor through actions which temporarily reduce the strength, duration, and frequency of uterine contractions. However, this effect is not consistent and may be offset by an increased rate of cervical dilation, which tends to shorten labor. Monitor neonates exposed to opioid analgesics during labor for signs of excess sedation and respiratory depression.

Data

Animal Data

Pregnant rats were treated with hydromorphone hydrochloride from Gestation Day 6 to 17 via oral gavage doses of 1, 5, or 10 mg/kg/day (0.4, 2, or 4 times the HDD of 24 mg based on body surface area, respectively). Maternal toxicity was noted in all treatment groups (reduced food consumption and body weights in the two highest dose groups). There was no evidence of malformations or embryotoxicity reported.

Pregnant rabbits were treated with hydromorphone hydrochloride from Gestation Day 7 to 19 via oral gavage doses of 10, 25, or 50 mg/kg/day (8.1, 20.3, or 40.5 times the HDD of 24 mg based on body surface area, respectively). Maternal toxicity was noted in the two highest dose groups (reduced food consumption and body weights). There was no evidence of malformations or embryotoxicity reported.

In a published study, neural tube defects (exencephaly and cranioschisis) were noted following subcutaneous administration of hydromorphone hydrochloride (19 to 258 mg/kg) on Gestation Day 8 to pregnant hamsters (6.4 to 87.2 times the HDD of 24 mg/day based on body surface area). The findings cannot be clearly attributed to maternal toxicity. No neural tube defects were noted at 14 mg/kg (4.7 times the human daily dose of 24 mg/day).

In a published study, CF-1 mice were treated subcutaneously with continuous infusion of 7.5, 15, or 30 mg/kg/day hydromorphone hydrochloride (1.5, 3, or 6.1 times the human daily dose of 24 mg based on body surface area) via implanted osmotic pumps during organogenesis (Gestation Days 7 to 10). Soft tissue malformations (cryptorchidism, cleft palate, malformed ventricles and retina), and skeletal variations (split supraoccipital, checkerboard and split sternebrae, delayed ossification of the paws, and ectopic ossification sites) were observed at doses 3 times the human dose of 24 mg/day based on body surface area. The findings cannot be clearly attributed to maternal toxicity.

Increased pup mortality and decreased pup body weights were noted at 0.8 and 2 times the human daily dose of 24 mg in a study in which pregnant rats were treated with hydromorphone hydrochloride from Gestation Day 7 to Lactation Day 20 via oral gavage doses of 0, 0.5, 2, or 5 mg/kg/day (0.2, 0.8, or 2 times the HDD of 24 mg based on body surface area, respectively). Maternal toxicity (decreased food consumption and body weight gain) was also noted at the two highest doses tested.

8.2 Lactation

Risk Summary

Low levels of opioid analgesics have been detected in human milk. The developmental and health benefits of breastfeeding should be considered along with the mother's clinical need for DILAUDID Oral Solution or DILAUDID Tablets and any potential adverse effects on the breastfed infant from DILAUDID Oral Solution or DILAUDID Tablets or from the underlying maternal condition.

Clinical Considerations

Monitor infants exposed to DILAUDID through breast milk for excess sedation and respiratory depression. Withdrawal symptoms can occur in breastfed infants when maternal administration of hydromorphone is stopped, or when breastfeeding is stopped.

8.3 Females and Males of Reproductive Potential

Infertility

Use of opioids for an extended period of time may cause reduced fertility in females and males of reproductive potential. It is not known whether these effects on fertility are reversible [see Adverse Reactions (6.2), Clinical Pharmacology (12.2), Nonclinical Toxicology (13.1)].

8.4 Pediatric Use

The safety and effectiveness of DILAUDID in pediatric patients have not been established.

8.5 Geriatric Use

Elderly patients (aged 65 years or older) may have increased sensitivity to hydromorphone. In general, use caution when selecting a dosage for an elderly patient, usually starting at the low end of the dosing range, reflecting the greater frequency of decreased hepatic, renal, or cardiac function and of concomitant disease or other drug therapy.

Respiratory depression is the chief risk for elderly patients treated with opioids, and has occurred after large initial doses were administered to patients who were not opioid-tolerant or when opioids were co-administered with other agents that depress respiration. Titrate the dosage of DILAUDID slowly in geriatric patients and frequently reevaluate the patient for signs of central nervous system and respiratory depression [see Warnings and Precautions (5.8)].

Hydromorphone is known to be substantially excreted by the kidney, and the risk of adverse reactions to this drug may be greater in patients with impaired renal function. Because elderly patients are more likely to have decreased renal function, care should be taken in dose selection, and it may be useful to regularly evaluate renal function.

8.6 Hepatic Impairment

The pharmacokinetics of hydromorphone is affected by hepatic impairment. Due to increased exposure of hydromorphone, patients with hepatic impairment should be started at one-fourth to one-half the recommended starting dose depending on the degree of hepatic dysfunction and regularly evaluated during dose titration. The pharmacokinetics of hydromorphone in patients with severe hepatic impairment has not been studied. A further increase in Cmax and AUC of hydromorphone in this group is expected and should be taken into consideration when selecting a starting dose [see Clinical Pharmacology (12.3)].

8.7 Renal Impairment

The pharmacokinetics of hydromorphone is affected by renal impairment. In addition, in patients with severe renal impairment, hydromorphone appeared to be more slowly eliminated with a longer terminal elimination half-life. Start patients with renal impairment on one-fourth to one-half the usual starting dose depending on the degree of impairment. Patients with renal impairment should be regularly evaluated during dose titration [see Clinical Pharmacology (12.3)].

9 DRUG ABUSE AND DEPENDENCE

9.1 Controlled Substance

DILAUDID Oral Solution and DILAUDID Tablets contain hydromorphone, a Schedule II controlled substance.

9.2 Abuse

DILAUDID Oral Solution and DILAUDID Tablets contain hydromorphone, a substance with high potential for misuse and abuse, which can lead to the development of substance use disorder, including addiction [see Warnings and Precautions (5.2)].

Misuse is the intentional use, for therapeutic purposes, of a drug by an individual in a way other than prescribed by a healthcare provider or for whom it was not prescribed.

Abuse is the intentional, non-therapeutic use of a drug, even once, for its desirable psychological or physiological effects.

Drug addiction is a cluster of behavioral, cognitive, and physiological phenomena that may include a strong desire to take the drug, difficulties in controlling drug use (e.g., continuing drug use despite harmful consequences, giving a higher priority to drug use than other activities and obligations), and possible tolerance or physical dependence.

Misuse and abuse of DILAUDID increases risk of overdose, which may lead to central nervous system and respiratory depression, hypotension, seizures, and death. The risk is increased with concurrent abuse of DILAUDID with alcohol and/or other CNS depressants. Abuse of and addiction to opioids in some individuals may not be accompanied by concurrent tolerance and symptoms of physical dependence. In addition, abuse of opioids can occur in the absence of addiction.

All patients treated with opioids require careful and frequent reevaluation for signs of misuse, abuse, and addiction, because use of opioid analgesic products carries the risk of addiction even under appropriate medical use. Patients at high risk of DILAUDID abuse include those with a history of prolonged use of any opioid, including products containing hydromorphone, those with a history of drug or alcohol abuse, or those who use DILAUDID in combination with other abused drugs.

"Drug-seeking" behavior is very common in persons with substance use disorders. Drug-seeking tactics include emergency calls or visits near the end of office hours, refusal to undergo appropriate examination, testing, or referral, repeated "loss" of prescriptions, tampering with prescriptions, and reluctance to provide prior medical records or contact information for other treating healthcare provider(s). "Doctor shopping" (visiting multiple prescribers to obtain additional prescriptions) is common among people who abuse drugs and people with substance use disorder. Preoccupation with achieving adequate pain relief can be appropriate behavior in a patient with inadequate pain control.

DILAUDID, like other opioids, can be diverted for nonmedical use into illicit channels of distribution. Careful record-keeping of prescribing information, including quantity, frequency, and renewal requests, as required by state and federal law, is strongly advised.

Proper assessment of the patient, proper prescribing practices, periodic reevaluation of therapy, and proper dispensing and storage are appropriate measures that help to limit abuse of opioid drugs.

Risks Specific to Abuse of DILAUDID

Abuse of DILAUDID Oral Solution or DILAUDID Tablets poses a risk of overdose and death. The risk is increased with concurrent use of DILAUDID with alcohol and/or other CNS depressants.

DILAUDID Oral Solution and DILAUDID Tablets are approved for oral use only.

Parenteral drug abuse is commonly associated with transmission of infectious diseases such as hepatitis and HIV.

9.3 Dependence

Both tolerance and physical dependence can develop during use of opioid therapy.

Tolerance is a physiological state characterized by a reduced response to a drug after repeated administration (i.e., a higher dose of a drug is required to produce the same effect that was once obtained at a lower dose).

Physical dependence is a state that develops as a result of a physiological adaptation in response to repeated drug use, manifested by withdrawal signs and symptoms after abrupt discontinuation or a significant dose reduction of a drug.

Withdrawal may be precipitated through the administration of drugs with opioid antagonist activity (e.g., naloxone, nalmefene), mixed agonist/antagonist analgesics (e.g., pentazocine, butorphanol, nalbuphine), or partial agonists (e.g., buprenorphine). Physical dependence may not occur to a clinically significant degree until after several days to weeks of continued use.

Do not rapidly reduce or abruptly discontinue DILAUDID Oral Solution and DILAUDID Tablets in a patient physically dependent on opioids. Rapid tapering of DILAUDID Oral Solution and DILAUDID Tablets in a patient physically dependent on opioids may lead to serious withdrawal symptoms, uncontrolled pain, and suicide. Rapid discontinuation has also been associated with attempts to find other sources of opioid analgesics, which may be confused with drug-seeking for abuse.

When discontinuing DILAUDID Oral Solution and DILAUDID Tablets, gradually taper the dosage using a patient-specific plan that considers the following: the dose of DILAUDID Oral Solution and DILAUDID Tablets the patient has been taking, the duration of treatment, and the physical and psychological attributes of the patient. To improve the likelihood of a successful taper and minimize withdrawal symptoms, it is important that the opioid tapering schedule is agreed upon by the patient. In patients taking opioids for an extended period of time at high doses, ensure that a multimodal approach to pain management, including mental health support (if needed), is in place prior to initiating an opioid analgesic taper [see Dosage and Administration (2.7), Warnings and Precautions (5.14)].

Infants born to mothers physically dependent on opioids will also be physically dependent and may exhibit respiratory difficulties and withdrawal signs [see Use in Specific Populations (8.1)].

10 OVERDOSAGE

Clinical Presentation

Acute overdose with hydromorphone can be manifested by respiratory depression, somnolence progressing to stupor or coma, skeletal muscle flaccidity, cold and clammy skin, constricted pupils, and, in some cases, pulmonary edema, bradycardia, hypotension, hypoglycemia, partial or complete airway obstruction, atypical snoring, and death. Marked mydriasis rather than miosis may be seen with hypoxia in overdose situations [see Clinical Pharmacology (12.2)]. Toxic leukoencephalopathy has been reported after opioid overdose and can present hours, days, or weeks after apparent recovery from the initial intoxication.

Treatment of Overdose

In case of overdose, priorities are the reestablishment of a patent and protected airway and institution of assisted or controlled ventilation, if needed. Employ other supportive measures (including oxygen and vasopressors) in the management of circulatory shock and pulmonary edema as indicated. Cardiac arrest or arrhythmias will require advanced life-support measures.

For clinically significant respiratory or circulatory depression secondary to opioid overdose, administer an opioid overdose reversal agent such as naloxone or nalmefene.

Because the duration of opioid reversal is expected to be less than the duration of action of hydromorphone in DILAUDID Oral Solution or DILAUDID Tablets, carefully monitor the patient until spontaneous respiration is reliably reestablished. If the response to an opioid overdose reversal agent is suboptimal or only brief in nature, administer additional reversal agent as directed by the product's prescribing information.

In an individual physically dependent on opioids, administration of the recommended usual dosage of the opioid overdose reversal agent will precipitate an acute withdrawal syndrome. The severity of the withdrawal symptoms experienced will depend on the degree of physical dependence and the dose of the reversal agent administered. If a decision is made to treat serious respiratory depression in the physically dependent patient, administration of the reversal agent should be initiated with care and by titration with smaller than usual doses of the reversal agent.

11 DESCRIPTION

DILAUDID (hydromorphone hydrochloride), a hydrogenated ketone of morphine, is an opioid agonist.

DILAUDID Tablets are supplied in 2 mg, 4 mg, and 8 mg tablets for oral administration. The tablet strengths describe the amount of hydromorphone hydrochloride in each tablet.

DILAUDID Oral Solution is supplied as 5 mg/5 mL (1 mg/mL) viscous liquid.

The chemical name is 4,5α-epoxy-3-hydroxy-17-methylmorphinan-6-one hydrochloride. The molecular weight is 321.80. Its molecular formula is C17H19NO3∙HCl, and it has the following chemical structure:

Hydromorphone hydrochloride is a white or almost white crystalline powder that is freely soluble in water, very slightly soluble in ethanol (96%), and practically insoluble in methylene chloride.

The 2 mg, 4 mg, and 8 mg tablets contain the following inactive ingredients: lactose anhydrous and magnesium stearate. DILAUDID Tablets may also contain traces of sodium metabisulfite.

The 2 mg tablets also contain D&C red #30 Lake dye and D&C yellow #10 Lake dye.

The 4 mg tablets also contain D&C yellow #10 Lake dye.

Each 5 mL (1 teaspoon) of DILAUDID Oral Solution contains 5 mg of hydromorphone hydrochloride. The inactive ingredients are purified water, methylparaben, propylparaben, sucrose, and glycerin. DILAUDID Oral Solution may contain traces of sodium metabisulfite.

12 CLINICAL PHARMACOLOGY

12.1 Mechanism of Action

Hydromorphone is a full opioid agonist and is relatively selective for the mu-opioid receptor, although it can bind to other opioid receptors at higher doses. The principal therapeutic action of hydromorphone is analgesia. Like all full opioid agonists, there is no ceiling effect for analgesia with morphine. Clinically, dosage is titrated to provide adequate analgesia and may be limited by adverse reactions, including respiratory and CNS depression.

The precise mechanism of the analgesic action is unknown. However, specific CNS opioid receptors for endogenous compounds with opioid-like activity have been identified throughout the brain and spinal cord and are thought to play a role in the analgesic effects of this drug.

12.2 Pharmacodynamics

Effects on the Central Nervous System

Hydromorphone produces respiratory depression by direct action on brain stem respiratory centers. The respiratory depression involves a reduction in the responsiveness of the brain stem respiratory centers to both increases in carbon dioxide tension and to electrical stimulation.

Hydromorphone causes miosis, even in total darkness. Pinpoint pupils are a sign of opioid overdose but are not pathognomonic (e.g., pontine lesions of hemorrhagic or ischemic origins may produce similar findings). Marked mydriasis rather than miosis may be seen due to hypoxia in overdose situations.

Effects on the Gastrointestinal Tract and Other Smooth Muscle

Hydromorphone causes a reduction in motility associated with an increase in smooth muscle tone in the antrum of the stomach and duodenum. Digestion of food in the small intestine is delayed and propulsive contractions are decreased. Propulsive peristaltic waves in the colon are decreased, while tone may be increased to the point of spasm, resulting in constipation. Other opioid-induced effects may include a reduction in biliary and pancreatic secretions, spasm of sphincter of Oddi, transient elevations in serum amylase, and opioid-induced esophageal dysfunction (OIED).

Effects on the Cardiovascular System

Hydromorphone produces peripheral vasodilation which may result in orthostatic hypotension or syncope. Manifestations of histamine release and/or peripheral vasodilation may include pruritus, flushing, red eyes and sweating, and/or orthostatic hypotension.

Effects on the Endocrine System

Opioids inhibit the secretion of adrenocorticotropic hormone (ACTH), cortisol, and luteinizing hormone (LH) in humans [see Adverse Reactions (6.2)]. They also stimulate prolactin, growth hormone (GH) secretion, and pancreatic secretion of insulin and glucagon.

Use of opioids for an extended period of time may influence the hypothalamic-pituitary-gonadal axis, leading to androgen deficiency that may manifest as low libido, impotence, erectile dysfunction, amenorrhea, or infertility. The causal role of opioids in the clinical syndrome of hypogonadism is unknown because the various medical, physical, lifestyle, and psychological stressors that may influence gonadal hormone levels have not been adequately controlled for in studies conducted to date [see Adverse Reactions (6.2)].

Effects on the Immune System

Opioids have been shown to have a variety of effects on components of the immune system in in vitro and animal models. The clinical significance of these findings is unknown. Overall, the effects of opioids appear to be modestly immunosuppressive.

Concentration–Efficacy Relationships

The minimum effective analgesic concentration will vary widely among patients, especially among patients who have been previously treated with opioid agonists. The minimum effective analgesic concentration of hydromorphone for any individual patient may increase over time due to an increase in pain, the development of a new pain syndrome, and/or the development of analgesic tolerance [see Dosage and Administration (2.1, 2.6)].

Concentration–Adverse Reaction Relationships

There is a relationship between increasing hydromorphone plasma concentration and increasing frequency of dose-related opioid adverse reactions such as nausea, vomiting, CNS effects, and respiratory depression. In opioid-tolerant patients, the situation may be altered by the development of tolerance to opioid-related adverse reactions [see Dosage and Administration (2.1, 2.3, 2.6)].

12.3 Pharmacokinetics

Absorption

The analgesic activity of DILAUDID (hydromorphone hydrochloride) is due to the parent drug, hydromorphone. Hydromorphone is rapidly absorbed from the gastrointestinal tract after oral administration and undergoes extensive first-pass metabolism. Exposure of hydromorphone (Cmax and AUC0-24) is dose-proportional at a dose range of 2 and 8 mg. In vivo bioavailability following single-dose administration of the 8 mg tablet is approximately 24% (coefficient of variation 21%). Bioequivalence between the DILAUDID 8 mg Tablet and an equivalent dose of DILAUDID Oral Solution has been demonstrated.

After oral administration of DILAUDID, peak plasma hydromorphone concentrations are generally attained within ½ to 1 hour.

Mean (%cv)
Dosage Form | Cmax (ng) | Tmax (hrs) | AUC (ng*hr/mL) | T ½ (hrs)
8 mg Tablet | 5.5 (33%) | 0.74 (34%) | 23.7 (28%) | 2.6 (18%)
8 mg Oral Liquid | 5.7 (31%) | 0.73 (71%) | 24.6 (29%) | 2.8 (20%)

Food Effects

In a study conducted with a single 8 mg dose of hydromorphone (2 mg hydromorphone immediate-release tablets), food lowered Cmax by 25%, prolonged Tmax by 0.8 hour, and increased AUC by 35%. The effects may not be clinically relevant.

Distribution

At therapeutic plasma levels, hydromorphone is approximately 8 to 19% bound to plasma proteins. After an intravenous bolus dose, the steady state of volume distribution [mean (% cv)] is 302.9 (32%) liters.

Elimination

The systemic clearance is approximately 1.96 (20%) liters/minute. The terminal elimination half-life of hydromorphone after an intravenous dose is about 2.3 hours.

Metabolism

Hydromorphone is extensively metabolized via glucuronidation in the liver, with greater than 95% of the dose metabolized to hydromorphone-3-glucuronide along with minor amounts of 6-hydroxy reduction metabolites.

Excretion

Only a small amount of the hydromorphone dose is excreted unchanged in the urine. Most of the dose is excreted as hydromorphone-3-glucuronide along with minor amounts of 6-hydroxy reduction metabolites.

Specific Populations

Hepatic Impairment

After oral administration of a single 4 mg dose (2 mg hydromorphone immediate-release tablets), mean exposure to hydromorphone (Cmax and AUC∞) is increased 4-fold in patients with moderate (Child-Pugh Group B) hepatic impairment compared with subjects with normal hepatic function. Due to increased exposure of hydromorphone, patients with moderate hepatic impairment should be started at a lower dose and closely monitored during dose titration. Pharmacokinetics of hydromorphone in severe hepatic impairment patients has not been studied. Further increase in Cmax and AUC of hydromorphone in this group is expected. As such, starting dose should be even more conservative [see Use in Specific Populations (8.6)].

Renal Impairment

After oral administration of a single 4 mg dose (2 mg hydromorphone immediate-release tablets), exposure to hydromorphone (Cmax and AUC0-48) is increased in patients with impaired renal function by 2-fold in moderate (CLcr = 40 to 60 mL/min) and 3-fold in severe (CLcr < 30 mL/min) renal impairment compared with normal subjects (CLcr > 80 mL/min). In addition, in patients with severe renal impairment hydromorphone appeared to be more slowly eliminated with longer terminal elimination half-life (40 hr) compared to patients with normal renal function (15 hr). Patients with moderate renal impairment should be started on a lower dose. Starting doses for patients with severe renal impairment should be even lower. Patients with renal impairment should be closely monitored during dose titration [see Use in Specific Populations (8.7)].

Age: Geriatric Population

In the geriatric population, age has no effect on the pharmacokinetics of hydromorphone.

Sex

Sex has little effect on the pharmacokinetics of hydromorphone. Females appear to have higher Cmax (25%) than males with comparable AUC0-24 values. The difference observed in Cmax may not be clinically relevant.

13 NONCLINICAL TOXICOLOGY

13.1 Carcinogenesis, Mutagenesis, Impairment of Fertility

Carcinogenesis

Long term studies in animals to evaluate the carcinogenic potential of hydromorphone have not been conducted.

Mutagenesis

Hydromorphone was positive in the mouse lymphoma assay in the presence of metabolic activation, but was negative in the mouse lymphoma assay in the absence of metabolic activation. Hydromorphone was not mutagenic in the in vitro bacterial reverse mutation assay (Ames assay). Hydromorphone was not clastogenic in either the in vitro human lymphocyte chromosome aberration assay or the in vivo mouse micronucleus assay.

Impairment of Fertility

Reduced implantation sites and viable fetuses were noted at 2.1 times the human daily dose of 32 mg/day in a study in which female rats were treated orally with 1.75, 3.5, or 7 mg/kg/day hydromorphone hydrochloride (0.5, 1.1, or 2.1 times a human daily dose of 24 mg/day (HDD) based on body surface area) beginning 14 days prior to mating through Gestation Day 7 and male rats were treated with the same hydromorphone hydrochloride doses beginning 28 days prior to and throughout mating.

14 CLINICAL STUDIES

Analgesic effects of single doses of DILAUDID Oral Solution administered to patients with post-surgical pain have been studied in double-blind controlled trials. In one study, both 5 mg and 10 mg of DILAUDID Oral Solution provided significantly more analgesia than placebo. In another trial, 5 mg and 10 mg of DILAUDID Oral Solution were compared to 30 mg and 60 mg of morphine sulfate oral liquid. The pain relief provided by 5 mg and 10 mg DILAUDID Oral Solution was comparable to 30 mg and 60 mg oral morphine sulfate, respectively.

16 HOW SUPPLIED/STORAGE AND HANDLING

DILAUDID is available as follows:

Oral Solution 5 mg/5 mL: a clear, colorless to pale yellow, slightly viscous liquid.
NDC 42858-416-16: Bottles of 1 pint (473 mL)

2 mg Tablets: light orange, round, flat-faced tablets, with beveled edges, debossed with a "P" on one side and the number "2" on the opposite side.
NDC 42858-122-01: Bottles of 100

4 mg Tablets: light yellow, round, flat-faced tablets, with beveled edges, debossed with a "P" on one side and the number "4" on the opposite side.
NDC 42858-234-01: Bottles of 100
NDC 42858-234-50: Bottles of 500

8 mg Tablets: white, triangular shaped tablets debossed with a "P" and an inverted "P" separated with a bisect on one side of the tablet and debossed with the number "8" on the other side of the tablet.
NDC 42858-338-01: Bottles of 100

STORAGE AND HANDLING

Store at 20° to 25°C (68° to 77°F) [see USP Controlled Room Temperature].

Protect from light.

Store DILAUDID Oral Solution and DILAUDID Tablets securely and dispose of properly.

17 PATIENT COUNSELING INFORMATION

Advise the patient to read the FDA-approved patient labeling (Medication Guide).

Storage and Disposal

Because of the risks associated with accidental ingestion, misuse, and abuse, advise patients to store DILAUDID Oral Solution and DILAUDID Tablets securely, out of sight and reach of children, and in a location not accessible by others, including visitors to the home. Inform patients that leaving DILAUDID Oral Solution and DILAUDID Tablets unsecured can pose a deadly risk to others in the home [see Warnings and Precautions (5.2, 5.3), Drug Abuse and Dependence (9.2)].

Advise patients and caregivers that when medicines are no longer needed, they should be disposed of promptly. Expired, unwanted, or unused DILAUDID Oral Solution and DILAUDID Tablets should be disposed of by flushing the unused medication down the toilet if a drug take-back option is not readily available. Inform patients that they can visit www.fda.gov/drugdisposal for a complete list of medicines recommended for disposal by flushing, as well as additional information on disposal of unused medicines.

Medication Errors

Instruct patients and caregivers how to measure and take or administer the correct dose of DILAUDID Oral Solution, and to always use a graduated oral syringe or measuring cup, with metric units of measurements (i.e., mL), to correctly measure the prescribed amount of medication. Inform patients and caregivers that oral dosing devices may be obtained from their pharmacy and to never use household teaspoons or tablespoons to measure DILAUDID Oral Solution [see Dosage and Administration (2.1), Warnings and Precautions (5.1)].

If the prescribed concentration is changed, instruct patients and caregivers on how to correctly measure the new dose to avoid errors which could result in accidental overdose and death.

Addiction, Abuse, and Misuse

Inform patients that the use of DILAUDID Oral Solution or DILAUDID Tablets, even when taken as recommended, can result in addiction, abuse, and misuse, which can lead to overdose and death [see Warnings and Precautions (5.2)]. Instruct patients not to share DILAUDID Oral Solution or DILAUDID Tablets with others and to take steps to protect DILAUDID Oral Solution or DILAUDID Tablets from theft or misuse.

Life-Threatening Respiratory Depression

Inform patients of the risk of life-threatening respiratory depression, including information that the risk is greatest when starting DILAUDID Oral Solution or DILAUDID Tablets or when the dosage is increased, and that it can occur even at recommended dosages.

Educate patients and caregivers on how to recognize respiratory depression and emphasize the importance of calling 911 or getting emergency medical help right away in the event of a known or suspected overdose [see Warnings and Precautions (5.3)].

Accidental Ingestion

Inform patients that accidental ingestion, especially by children, may result in respiratory depression or death [see Warnings and Precautions (5.3)].

Interactions with Benzodiazepines and Other CNS Depressants

Inform patients and caregivers that potentially fatal additive effects may occur if DILAUDID Oral Solution or DILAUDID Tablets are used with benzodiazepines or other CNS depressants, including alcohol (e.g., non-benzodiazepine sedative/hypnotics, anxiolytics, tranquilizers, muscle relaxants, general anesthetics, antipsychotics, gabapentinoids [gabapentin or pregabalin], and other opioids), and not to use these concomitantly unless supervised by a healthcare provider [see Warnings and Precautions (5.4), Drug Interactions (7)].

Patient Access to an Opioid Overdose Reversal Agent for the Emergency Treatment of Opioid Overdose

Inform patients and caregivers about opioid overdose reversal agents (e.g., naloxone, nalmefene). Discuss the importance of having access to an opioid overdose reversal agent, especially if the patient has risk factors for overdose (e.g., concomitant use of CNS depressants, a history of opioid use disorder, or prior opioid overdose) or if there are household members (including children) or other close contacts at risk for accidental ingestion or opioid overdose.

Discuss with the patient the options for obtaining an opioid overdose reversal agent (e.g., prescription, over-the-counter, or as part of a community-based program) [see Dosage and Administration (2.2), Warnings and Precautions (5.3)].

Educate patients and caregivers on how to recognize the signs and symptoms of an overdose.

Explain to patients and caregivers that effects of opioid overdose reversal agents like naloxone and nalmefene are temporary, and that they must call 911 or get emergency medical help right away in all cases of known or suspected opioid overdose, even if an opioid overdose reversal agent is administered [see Overdosage (10)].

Advise patients and caregivers:

- how to treat with the overdose reversal agent in the event of an opioid overdose
- to tell family and friends about the opioid overdose reversal agent, and to keep it in a place where family and friends can access it in an emergency
- to read the Patient Information (or other educational material) that will come with their opioid overdose reversal agent. Emphasize the importance of doing this before an opioid emergency happens, so the patient and caregiver will know what to do.

Hyperalgesia and Allodynia

Inform patients and caregivers not to increase opioid dosage without first consulting a clinician. Advise patients to seek medical attention if they experience symptoms of hyperalgesia, including worsening pain, increased sensitivity to pain, or new pain [see Warnings and Precautions (5.7), Adverse Reactions (6.2)].

Serotonin Syndrome

Inform patients that DILAUDID could cause a rare but potentially life-threatening condition called serotonin syndrome resulting from concomitant administration of serotonergic drugs. Warn patients of the symptoms of serotonin syndrome and to seek medical attention right away if symptoms develop. Instruct patients to inform their healthcare providers if they are taking, or plan to take, serotonergic medications [see Drug Interactions (7)].

MAOI Interaction

Inform patients to avoid taking DILAUDID Oral Solution or DILAUDID Tablets while using any drugs that inhibit monoamine oxidase. Patients should not start MAOIs while taking DILAUDID Oral Solution or DILAUDID Tablets [see Drug Interactions (7)].

Important Administration Instructions

Instruct patients how to properly take DILAUDID [see Dosage and Administration (2), Warnings and Precautions (5.1)].

- Instruct patients and caregivers on how to accurately measure and take the correct dose of DILAUDID Oral Solution.
- Strongly advise patients and caregivers to always use a graduated oral dosing syringe or measuring cup with metric units of measurements (i.e., mL) to correctly measure the prescribed amount of medication.
- Inform patients and caregivers that oral dosing devices may be obtained from their pharmacy and to never use household teaspoons or tablespoons to measure DILAUDID Oral Solution [see Dosage and Administration (2)].
- Advise patients and caregivers not to adjust the dose of DILAUDID Oral Solution without consulting with a physician or other healthcare professional.

Important Discontinuation Instructions

In order to avoid developing withdrawal symptoms, instruct patients not to discontinue DILAUDID Oral Solution or DILAUDID Tablets without first discussing a tapering plan with the prescriber [see Dosage and Administration (2.7)].

Driving or Operating Heavy Machinery

Inform patients that DILAUDID Oral Solution or DILAUDID Tablets may impair the ability to perform potentially hazardous activities such as driving a car or operating heavy machinery. Advise patients not to perform such tasks until they know how they will react to the medication [see Warnings and Precautions (5.15)].

Constipation

Advise patients of the potential for severe constipation, including management instructions and when to seek medical attention [see Adverse Reactions (6), Clinical Pharmacology (12.2)].

Healthcare professionals can telephone Rhodes Pharmaceuticals Medical Services Department (1-888-827-0616) for information on this product.

Adrenal Insufficiency

Inform patients that opioids could cause adrenal insufficiency, a potentially life-threatening condition. Adrenal insufficiency may present with non-specific symptoms and signs such as nausea, vomiting, anorexia, fatigue, weakness, dizziness, and low blood pressure. Advise patients to seek medical attention if they experience a constellation of these symptoms [see Warnings and Precautions (5.9)].

Hypotension

Inform patients that DILAUDID Oral Solution or DILAUDID Tablets may cause orthostatic hypotension and syncope. Instruct patients how to recognize symptoms of low blood pressure and how to reduce the risk of serious consequences should hypotension occur (e.g., sit or lie down, carefully rise from a sitting or lying position) [see Warnings and Precautions (5.10)].

Anaphylaxis

Inform patients that anaphylaxis has been reported with ingredients contained in DILAUDID Oral Solution or DILAUDID Tablets. Advise patients how to recognize such a reaction and when to seek medical attention [see Contraindications (4), Adverse Reactions (6)].

Pregnancy

Neonatal Opioid Withdrawal Syndrome

Inform female patients of reproductive potential that use of DILAUDID Oral Solution or DILAUDID Tablets for an extended period of time during pregnancy can result in neonatal opioid withdrawal syndrome, which may be life-threatening if not recognized and treated [see Warnings and Precautions (5.5), Use in Specific Populations (8.1)].

Embryo-Fetal Toxicity

Inform female patients of reproductive potential that DILAUDID Oral Solution or DILAUDID Tablets can cause fetal harm and to inform their healthcare provider of a known or suspected pregnancy [see Use in Specific Populations (8.1), Warnings and Precautions (5.5)].

Lactation

Advise nursing mothers to carefully observe infants for increased sleepiness (more than usual), breathing difficulties, or limpness. Instruct nursing mothers to seek immediate medical care if they notice these signs [see Use in Specific Populations (8.2)].

Infertility

Inform patients that use of opioids for an extended period of time may cause reduced fertility. It is not known whether these effects on fertility are reversible [see Use in Specific Population (8.3)].

Manufactured by:
Purdue Pharma L.P.
Stamford, CT 06901

Marketed by:
Rhodes Pharmaceuticals
Wilson, NC 27893

xxxxxx-0x

Revised: 12/2025

Medication Guide
DILAUDID® (dī-law-did)
(hydromorphone hydrochloride) Tablets and Oral Solution, CII

DILAUDID Tablets and DILAUDID Oral Solution are:

- Strong prescription pain medicines that contain an opioid (narcotic) that is used to manage pain severe enough to require an opioid analgesic, when other pain treatments such as non-opioid pain medicines do not treat your pain well enough or you cannot tolerate them.
- Opioid pain medicines that can put you at risk for overdose and death. Even if you take your dose correctly as prescribed, you are at risk for opioid addiction, abuse, and misuse that can lead to death.

Important information about DILAUDID:

- Get emergency help or call 911 right away if you take too much DILAUDID Tablets or DILAUDID Oral Solution (overdose). When you first start taking DILAUDID Tablets or DILAUDID Oral Solution, when your dose is changed, or if you take too much (overdose), serious or life-threatening breathing problems that can lead to death may occur. Ask your healthcare provider about medicines like naloxone or nalmefene that can be used in an emergency to reverse an opioid overdose.
- Taking DILAUDID Tablets or DILAUDID Oral Solution with other opioid medicines, benzodiazepines, gabapentinoids (gabapentin or pregabalin), alcohol, or other central nervous system depressants (including street drugs) can cause severe drowsiness, decreased awareness, breathing problems, coma, and death.
- Never give anyone else your DILAUDID Tablets or DILAUDID Oral Solution. They could die from taking it. Selling or giving away DILAUDID Tablets or DILAUDID Oral Solution is against the law.
- Store DILAUDID Tablets or DILAUDID Oral Solution securely, out of sight and reach of children, and in a location not accessible by others, including visitors to the home.

Do not take DILAUDID Tablets or DILAUDID Oral Solution if you have:

- Severe asthma, trouble breathing, or other lung problems.
- A bowel blockage or have narrowing of the stomach or intestines.

Before taking DILAUDID Tablets or DILAUDID Oral Solution, tell your healthcare provider if you have a history of:

- head injury, seizures
- problems urinating

- liver, kidney, thyroid problems
- pancreas or gallbladder problems

- abuse of street or prescription drugs, alcohol addiction, opioid overdose, or mental health problems

Tell your healthcare provider if you are:

- Noticing your pain getting worse. If your pain gets worse after you take DILAUDID, do not take more of DILAUDID without first talking to your healthcare provider. Talk to your healthcare provider if the pain that you have increases, if you feel more sensitive to pain, or if you have new pain after taking DILAUDID.
- Pregnant or planning to become pregnant. Use of DILAUDID Tablets and DILAUDID Oral Solution for an extended period of time during pregnancy can cause withdrawal symptoms in your newborn baby that could be life-threatening if not recognized and treated.
- Breastfeeding. DILAUDID Tablets and DILAUDID Oral Solution pass into breast milk and may harm your baby. Carefully observe infants for increased sleepiness (more than usual), breathing difficulties, or limpness. Seek immediate medical care if you notice these signs.
- Living in a household where there are small children or someone who has abused street or prescription drugs.
- Taking prescription or over-the-counter medicines, vitamins, or herbal supplements. Taking DILAUDID with certain other medicines can cause serious side effects that could lead to death.

When taking DILAUDID:

- Do not change your dose. Take DILAUDID exactly as prescribed by your healthcare provider. Use the lowest dose possible for the shortest time needed.
- For acute (short-term) pain, you may only need to take DILAUDID for a few days. You may have some DILAUDID left over that you did not use. See disposal information at the bottom of this section for directions on how to safely throw away (dispose of) your unused DILAUDID.
- Do not take more than your prescribed dose. If you miss a dose, take your next dose at your usual time.
- Call your healthcare provider if the dose you are taking does not control your pain.
- If you have been taking DILAUDID Tablets or DILAUDID Oral Solution regularly, do not stop taking DILAUDID Tablets or DILAUDID Oral Solution without talking to your healthcare provider.
- Dispose of expired, unwanted, or unused DILAUDID Tablets or DILAUDID Oral Solution by promptly flushing down the toilet, if a drug take-back option is not readily available. Visit www.fda.gov/drugdisposal for additional information on disposal of unused medicines.

While taking DILAUDID, DO NOT:

- Drive or operate heavy machinery until you know how DILAUDID Tablets or DILAUDID Oral Solution affect you. DILAUDID can make you sleepy, dizzy, or lightheaded.
- Drink alcohol or use prescription or over-the-counter medicines that contain alcohol. Using products containing alcohol during treatment with DILAUDID Tablets or DILAUDID Oral Solution may cause you to overdose and die.

The possible side effects of DILAUDID Tablets and DILAUDID Oral Solution:

- Constipation, nausea, sleepiness, vomiting, tiredness, headache, dizziness, abdominal pain. Call your healthcare provider if you have any of these symptoms and they are severe.

Get emergency medical help or call 911 right away if you have:

- Trouble breathing, shortness of breath, fast heartbeat, chest pain, swelling of your face, tongue, or throat, extreme drowsiness, light-headedness when changing positions, feeling faint, agitation, high body temperature, trouble walking, stiff muscles, or mental changes such as confusion.

These are not all the possible side effects of DILAUDID Tablets and DILAUDID Oral Solution. Call your healthcare provider for medical advice about side effects. You may report side effects to FDA at 1-800-FDA-1088. For more information, go to dailymed.nlm.nih.gov
Marketed by: Rhodes Pharmaceuticals, Wilson, NC 27893 US, http://rhodespharma.com or call 1-888-827-0616

This Medication Guide has been approved by the U.S. Food and Drug Administration.

Revised: 12/2025

PRINCIPAL DISPLAY PANEL - 2 mg Tablet Bottle Label

NDC 42858-122-01

Dilaudid®
(hydromorphone HCl)
Tablets, USP
CII

2 mg
Rx only

Dispense the accompanying
Medication Guide to each patient.

Rhodes

100 Tablets

PRINCIPAL DISPLAY PANEL - 4 mg Tablet Bottle Label

NDC 42858-234-01

Dilaudid®
(hydromorphone HCl)
Tablets, USP
CII

4 mg
Rx only

Dispense the accompanying
Medication Guide to each patient.

Rhodes

100 Tablets

PRINCIPAL DISPLAY PANEL - 8 mg Tablet Bottle Label

NDC 42858-338-01

Dilaudid®
(hydromorphone HCl)
Tablets, USP
CII

8 mg
Rx only

Dispense the accompanying
Medication Guide to each patient.

Rhodes

100 Tablets

PRINCIPAL DISPLAY PANEL - 473 mL Bottle Label

NDC 42858-416-16

Dilaudid®
(hydromorphone HCl)
Oral Solution, USP
CII

5 mg/5 mL
(1 mg/mL)

One Pint (473 mL)

Dispense the accompanying
Medication Guide to each patient.

Rhodes
Rx only